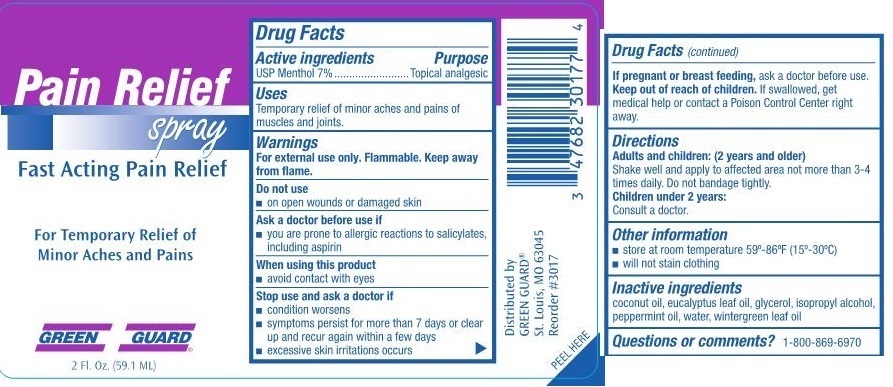 DRUG LABEL: Pain Relief
NDC: 47682-321 | Form: SPRAY
Manufacturer: Unifirst First Aid Corporation
Category: otc | Type: HUMAN OTC DRUG LABEL
Date: 20250908

ACTIVE INGREDIENTS: MENTHOL 70 mg/1 L
INACTIVE INGREDIENTS: COCONUT OIL; ISOPROPYL ALCOHOL; EUCALYPTUS OIL; GLYCERIN; WATER; METHYL SALICYLATE; PEPPERMINT OIL

Pain Relief Spray Green Guard

Active ingredients

USP Menthol 7%

Purpose

Topical analgesic

Uses

Temporary relief of minor aches and pains of muscles and joints.

Warnings

For external use only. Flammable. Keep away from flame.

Do not use

- on open wounds or damaged skin

Ask a doctor before use if

- you are prone to allergic reactions to salicylates, including aspirin

When using this product

- avoid contact with eyes

Stop use and ask a doctor if

- condition worsens
- symptoms persist for more than 7 days or clear up and recur again within a few days
- excessive skin irritation occurs

If pregnant or breast feeding,

ask a doctor before use.

Keep out of reach of children.

If swallowed, get medical help or contact a Poison Control Center right away.

Directions

Adults and children (2 years and older):

Shake well and aply to affected araea not more than 3-4 times daily.

Do not bandage tightly.

Children under 2 years:

Consult a doctor

Other information

- store at room temperature 56°-86°F (15°-30°C)
- will not stain clothing

Inactive ingredients

coconut oil, eucalyptus lkeaf oil, glycerol, isopropyl alcohol, peppermint oil, water, wintergreen leaf oil

Questions or comments?

1-800-869-6970

Green Guard Pain Relief Spray Label

Pain Relief spray

Fast Acting pain Relief

For Temporary Relief of Minor Aches and Pains

Green Guard®

2 Fl. Oz. (59.1 mL)